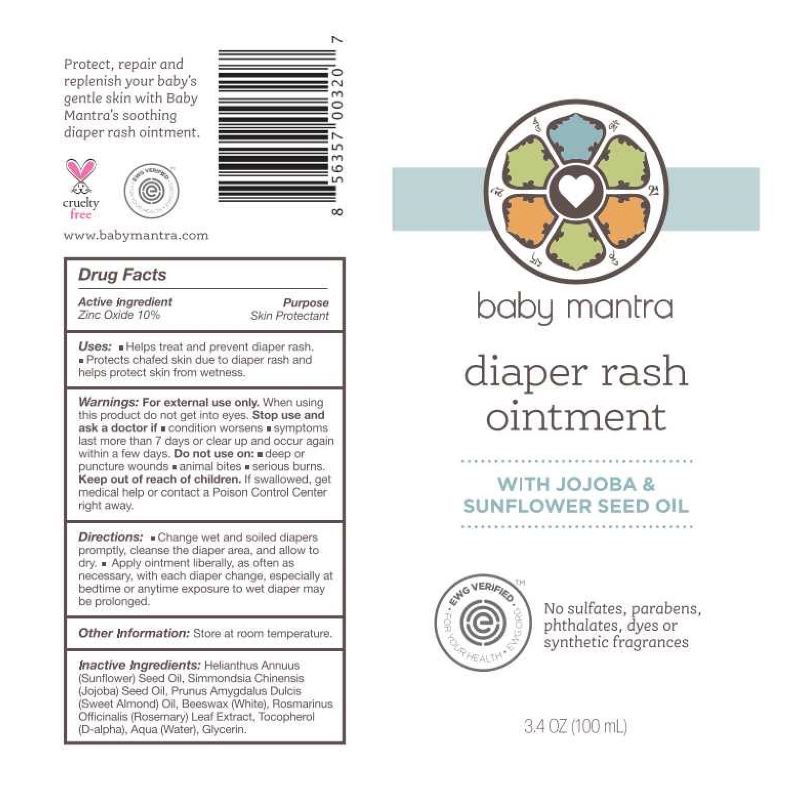 DRUG LABEL: Baby Mantra Diaper Cream
NDC: 76348-825 | Form: OINTMENT
Manufacturer: Renu Laboratories, LLC
Category: otc | Type: HUMAN OTC DRUG LABEL
Date: 20250414

ACTIVE INGREDIENTS: ZINC OXIDE 10 g/100 mL
INACTIVE INGREDIENTS: ALMOND OIL; .ALPHA.-TOCOPHEROL, D-; GLYCERIN; JOJOBA OIL; WHITE WAX; WATER; ROSEMARY; SUNFLOWER OIL

Baby Mantra Diaper Rash Ointment

Active Ingredient

Zinc Oxide 10%

Purpose

Skin Protectant

Uses:

- Helps treat and prevent diaper rash.
- Protects chafed skin due to diaper rash and helps protect skin from wetness.
- Helps prevent and temporarily protects chafed, chapped, cracked or wind-burned skin and lips.

Warnings: For external use only.

When using this product, do not get into eyes.

Stop use and ask a doctor if

- condition worsens
- symptoms last more than 7 days or clear up and occur again within a few days

Do not use on:

- deep or puncture wounds
- animal bites
- serious burns

Keep out of reach of children. If swallowed, get medical help or contact a Poison Control Center right away.

Stop use and ask a doctor if

- condition worsens
- symptoms last more than 7 days or clear up and occur again within a few days

Do not use on:

- deep or puncture wounds
- animal bites
- serious burns

Keep out of reach of children. If swallowed, get medical help or contact a Poison Control Center right away.

Directions:

- Change wet and soiled diapers promptly, cleanse the diaper area, and allow to dry.
- Apply ointment liberally, as often as necessary, with each diaper change, especially at bedtime or anytime exposure to wet diaper

Inactive Ingredients:

Helianthus Annuus (Sunflower) Seed Oil, Simmondsia Chinensis (Jojoba) Seed Oil, Prunus Amygdalus Dulcis (Sweet Almond) Oil, Beeswax (White), Rosmarinus Officinalis (Rosemary) Leaf Extract, Tocopherol (D-alpha), Aqua (Water), Glycerin

OTHER SAFETY INFORMATION

Store at room temperature

RECENT MAJOR CHANGES

For Indications and Usage section : Not a major change - We have only updated our Effective Date.

For Dosage and Administration section: Not a major change - we have only updated our Effective Date.

PACKAGE LABEL

TUBE ARTWORK